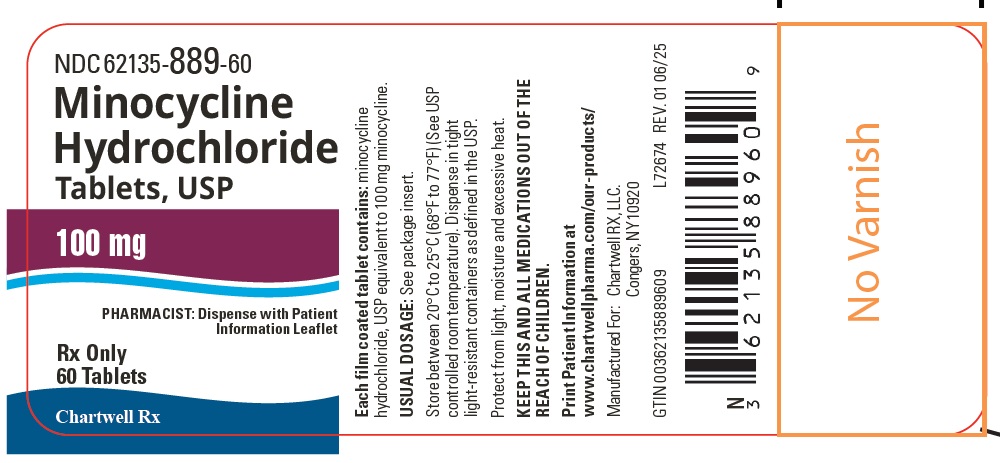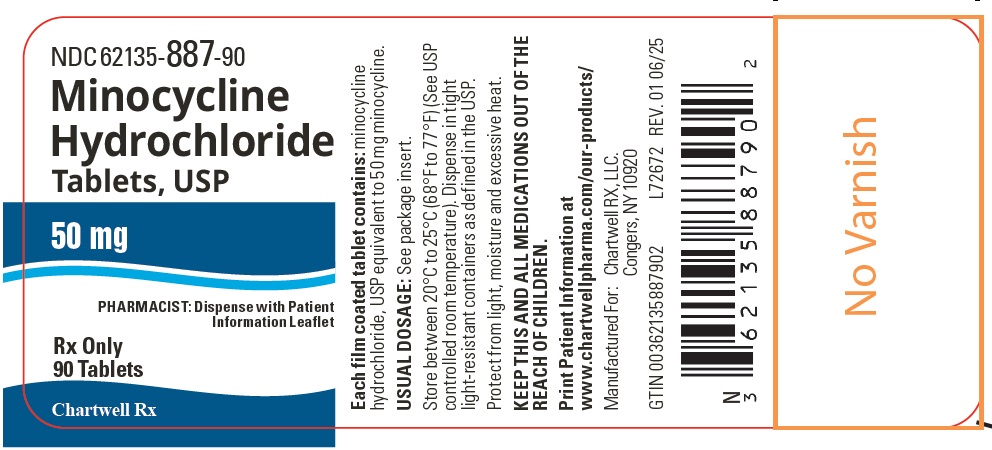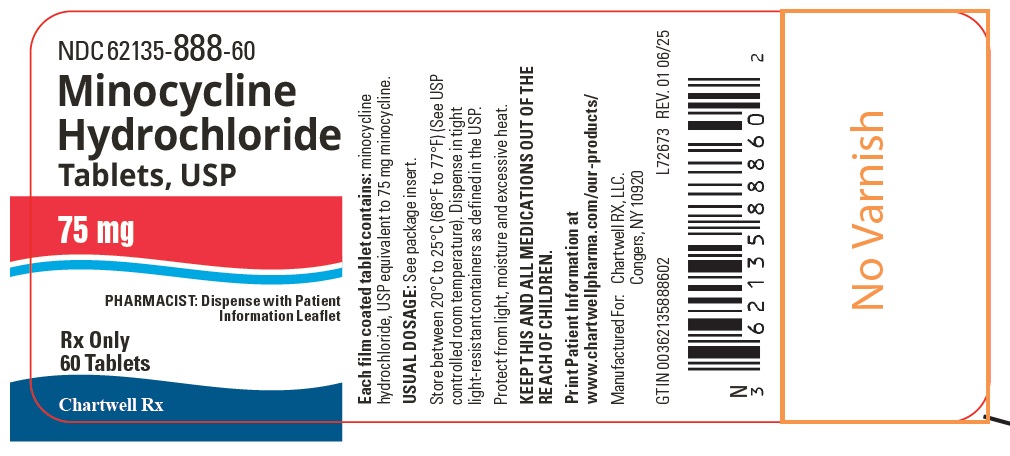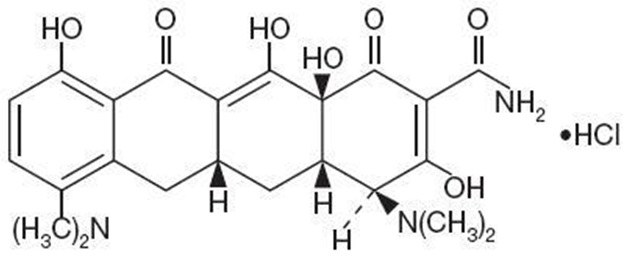 DRUG LABEL: Minocycline Hydrochloride
NDC: 62135-887 | Form: TABLET
Manufacturer: Chartwell RX, LLC
Category: prescription | Type: HUMAN PRESCRIPTION DRUG LABEL
Date: 20250617

ACTIVE INGREDIENTS: MINOCYCLINE HYDROCHLORIDE 50 mg/1 1
INACTIVE INGREDIENTS: LACTOSE MONOHYDRATE; MICROCRYSTALLINE CELLULOSE; SODIUM STARCH GLYCOLATE TYPE A; POVIDONE, UNSPECIFIED; POLYSORBATE 80; MAGNESIUM STEARATE; POLYETHYLENE GLYCOL 400; TITANIUM DIOXIDE; HYPROMELLOSE, UNSPECIFIED

Minocycline Hydrochloride Tablets, USP
Rx Only

To reduce the development of drug-resistant bacteria and maintain the effectiveness of minocycline hydrochloride tablets and other antibacterial drugs, minocycline hydrochloride tablets should be used only to treat or prevent infections that are proven or strongly suspected to be caused by bacteria.

DESCRIPTION

Minocycline Hydrochloride, USP a semisynthetic derivative of tetracycline, is 4,7-Bis(dimethylamino)-1,4,4a,5,5a,6,11,12a-octahydro-3,10,12,12a-tetrahydroxy-1,11-dioxo-2-naphthacenecarboxamide monohydrochloride. Its structural formula is:

C23H27N3O7•HCL M.W. 493.94

Minocycline Hydrochloride Tablets, USP for oral administration contain minocycline HCl equivalent to 50 mg, 75 mg or 100 mg of minocycline. In addition, 50 mg, 75 mg and 100 mg tablets contain the following inactive ingredients: lactose monohydrate, magnesium stearate, microcrystalline cellulose, povidone, sodium starch glycolate, titanium dioxide, hypromellose, polyethylene glycol 400, and polysorbate 80.

CLINICAL PHARMACOLOGY

Following a single dose of one 100 mg tablet of minocycline hydrochloride administered to 28 normal fasting adult volunteers, maximum serum concentrations were attained in 1 to 3 hours (average 1.71 hours) and ranged from 491.71 to 1292.70 ng/mL (average 758.29 ng/mL). The serum half-life in the normal volunteers ranged from 11.38 to 24.31 hours (average 17.03 hours).

When minocycline hydrochloride tablets were given concomitantly with a meal, which included dairy products, the extent of absorption of minocycline hydrochloride tablets was slightly decreased (6%). The peak plasma concentrations were slightly decreased (12%) and delayed by 1.09 hours when administered with food, compared to dosing under fasting conditions. Minocycline HCl may be administered with or without food.

In previous studies with other minocycline dosage forms, the minocycline serum half-life ranged from 11 to 16 hours in 7 patients with hepatic dysfunction, and from 18 to 69 hours in 5 patients with renal dysfunction. The urinary and fecal recovery of minocycline when administered to 12 normal volunteers was one-half to one-third that of other tetracyclines.

Microbiology

The tetracyclines are primarily bacteriostatic and are thought to exert their antimicrobial effect by the inhibition of protein synthesis. The tetracyclines, including minocycline, have similar antimicrobial spectra of activity against a wide range of gram-positive and gram-negative organisms. Cross-resistance of these organisms to tetracyclines is common.

Minocycline has been shown to be active against most strains of the following microorganisms, both in vitro and in clinical infections as described in the INDICATIONS AND USAGEsection:

AEROBIC GRAM-POSITIVE MICROORGANISMS

Because many strains of the following gram-positive microorganisms have been shown to be resistant to tetracyclines, culture and susceptibility testing are especially recommended. Tetracycline antibiotics should not be used for streptococcal diseases unless the organism has been demonstrated to be susceptible. Tetracyclines are not the drug of choice in the treatment of any type of staphylococcal infection.

Bacillus anthracisa

Listeria monocytogenesa

Staphylococcus aureus

Streptococcus pneumoniae

AEROBIC GRAM-NEGATIVE MICROORGANISMS

Bartonella bacilliformis

Brucella species

Calymmatobacterium granulomatis

Campylobacter fetus

Francisella tularensis

Haemophilus ducreyi

Vibrio cholerae

Yersinia pestis

Because many strains of the following groups of gram-negative microorganisms have been shown to be resistant to tetracyclines, culture and susceptibility tests are especially recommended.

Acinetobacter species

Enterobacter aerogenes

Escherichia coli

Haemophilus influenzae

Klebsiella species

Neisseria gonorrhoeaea

Neisseria meningitidisa

Shigella species

“OTHER” MICROORGANISMS

Actinomyces speciesa

Borrelia recurrentis

Chlamydia psittaci

Chlamydia trachomatis

Clostridium speciesa

Entamoeba species

Fusobacterium nucleatum subspecies fusiformea

Mycobacterium marinum

Mycoplasma pneumoniae

Propionibacterium acnes

Rickettsiae

Treponema pallidum subspecies palliduma

Treponema pallidum subspecies pertenuea

Ureaplasma urealyticum

aWhen penicillin is contraindicated, tetracyclines are alternative drugs in the treatment of infections caused by the cited microorganisms.

Susceptibility Tests

Susceptibility testing should be performed with tetracycline since it predicts susceptibility to minocycline. However, certain organisms (e.g., some staphylococci, and Acinetobacter species) may be more susceptible to minocycline and doxycycline than tetracycline.

Dilution Techniques

Quantitative methods are used to determine antimicrobial minimal inhibitory concentrations (MICs). These MICs provide estimates of the susceptibility of bacteria to antimicrobial compounds. The MICs should be determined using a standardized procedure. Standardized procedures are based on a dilution method^1,3(broth or agar) or equivalent with standardized inoculum concentrations and standardized concentrations of tetracycline powder. The MIC values should be interpreted according to the following criteria:

For testing aerobic gram-negative microorganisms (Enterobacteriaceae), Acinetobacter species and Staphylococcus aureus:

MIC (mcg/mL) | Interpretation
≤ 4 | Susceptible (S)
8 | Intermediate (I)
≥ 16 | Resistant (R)

For testing Haemophilus influenzaeband Streptococcus pneumoniaec:

MIC (mcg/mL) | Interpretation
≤ 2 | Susceptible (S)
4 | Intermediate (I)
≥ 8 | Resistant (R)

b. These interpretative standards are applicable only to broth microdilution susceptibility testing with Haemophilus influenzae using Haemophilus Test Medium.^1

c. These interpretative standards are applicable only to broth microdilution susceptibility testing using cation-adjusted Muller-Hinton broth with 2 to 5% lysed horse blood.^1

For testing Neisseria gonorrhoeaed:

MIC (mcg/mL) | Interpretation
≤ 0.25 | Susceptible (S)
0.5-1 | Intermediate (I)
≥ 2 | Resistant (R)

d. These interpretative standards are applicable only to agar dilution susceptibility testing using GC agar base and 1% defined growth supplements.^1

A report of “Susceptible” indicates that the pathogen is likely to be inhibited if the antimicrobial compound in the blood reaches the concentrations usually achievable. A report of “Intermediate” indicates that the result should be considered equivocal, and, if the microorganism is not fully susceptible to alternative, clinically feasible drugs, the test should be repeated. This category implies possible clinical applicability in body sites where the drug is physiologically concentrated or in situations where high dosage of drug can be used. This category also provides a buffer zone which prevents small uncontrolled technical factors from causing major discrepancies in interpretation. A report of “Resistant” indicates that the pathogen is not likely to be inhibited if the antimicrobial compound in the blood reaches the concentrations usually achievable; other therapy should be selected.

Standardized susceptibility test procedures require the use of laboratory control microorganisms to control the technical aspects of the laboratory procedures. Standard tetracycline powder should provide the following MIC values:

Microorganism |  | MIC (mcg/mL)
Escherichia coli Enterococcus faecalis Staphylococcus aureus Haemophilus influenzae Streptococcus pneumoniae Neisseria gonorrhoeae | ATCC 25922 ATCC 29212 ATCC 29213 ATCC 49247 ATCC 49619 ATCC 49226 | 0.5-2; 8-32; 0.25-1; 4-32; 0.12-0.5; 0.25-1

Diffusion techniques:

Quantitative methods that require measurement of zone diameters also provide reproducible estimates of the susceptibility of bacteria to antimicrobial compounds. One such standardized procedure^2,3requires the use of standardized inoculum concentrations. This procedure uses paper disks impregnated with 30 mcg tetracycline (class disk) or 30 mcg minocycline to test the susceptibility of microorganisms to minocycline.

Reports from the laboratory providing results of the standard single-disk susceptibility test with a 30 mcg tetracycline or minocycline disk should be interpreted according to the following criteria:

For testing aerobic gram-negative microorganisms (Enterobacteriaceae). Acinetobacter species and Staphylococcus aureus:

Zone Diameter (mm) | Interpretation
≥ 19 | Susceptible (S)
15-18 | Intermediate (I)
≤ 14 | Resistant (R)

For testing Haemophilus influenzaee:

Zone Diameter (mm) | Interpretation
≥ 29 | Susceptible (S)
26-28 | Intermediate (I)
≤ 25 | Resistant (R)

e. These zone diameter standards are applicable only to susceptibility testing with Haemophilus influenzaeusing Haemophilus Test Medium and a 30 mcg tetracycline disk.^2

For testing Neisseria gonorrhoeaef:

Zone Diameter (mm) | Interpretation
≥ 38 | Susceptible (S)
31-37 | Intermediate (I)
≤ 30 | Resistant (R)

f. These interpretative standards are applicable only to disk diffusion testing using GC agar and 1% growth supplements, and a 30 mcg tetracycline disk.^2

For testing Streptococcus pneumoniaeg:

Zone Diameter (mm) | Interpretation
≥ 23 | Susceptible (S)
19-22 | Intermediate (I)
≤ 18 | Resistant (R)

g. These interpretative standards are applicable only to disk diffusion testing using Muller-Hinton agar adjusted with 5% sheep blood and a 30 mcg tetracycline-class disk.^2

For testing Vibrio choleraeh:

Zone Diameter (mm) | Interpretation
≥ 19 | Susceptible (S)
15-18 | Intermediate (I)
≤ 14 | Resistant (R)

h. These interpretative standards are applicable only to disk diffusion testing performed with a 30 mcg tetracycline-class disk.^2

Interpretation should be as stated above for results using dilution techniques. Interpretation involves correlation of the diameter obtained in the disk test with the MIC for tetracycline.

As with standardized dilution techniques, diffusion methods require the use of laboratory control microorganisms that are used to control the technical aspects of the laboratory procedures. For the diffusion technique, the 30 mcg tetracycline or minocycline disk should provide the following zone diameters in these laboratory test quality control strains:

Microorganism |  | Zone Diameter Range (mm)
 |  | Tetracycline | Minocycline
Escherichia coli Staphylococcus aureus Haemophilus influenzae Neisseria gonorrhoeae Streptococcus pneumoniae | ATCC 25922 ATCC 29213 ATCC 49247 ATCC 49226 ATCC 49619 | 18-25 24-30 14-22 30-42 27-31 | 19-25 25-30 — — —

INDICATIONS AND USAGE

Minocycline hydrochloride tablets are indicated in the treatment of the following infections due to susceptible strains of the designated microorganisms:

- Rocky Mountain spotted fever, typhus fever and the typhus group, Q fever, rickettsialpox and tick fevers caused by Rickettsiae.
- Respiratory tract infections caused by Mycoplasma pneumoniae.
- Lymphogranuloma venereum caused by Chlamydia trachomatis.
- Psittacosis (Ornithosis) due to Chlamydia psittaci.
- Trachoma caused by Chlamydia trachomatis, although the infectious agent is not always eliminated, as judged by immunoflourescence.
- Inclusion conjunctivitis caused by Chlamydia trachomatis.
- Nongonococcal urethritis, endocervical, or rectal infections in adults caused by Ureaplasma urealyticum or Chlamydia trachomatis.
- Relapsing fever due to Borrelia recurrentis.
- Chancroid caused by Haemophilus ducreyi.
- Plague due to Yersinia pestis.
- Tularemia due to Francisella tularensis.
- Cholera caused by Vibrio cholerae.
- Campylobacter fetus infections caused by Campylobacter fetus.
- Brucellosis due to Brucella species (in conjunction with streptomycin).
- Bartonellosis due to Bartonella bacilliformis.
- Granuloma inguinale caused by Calymmatobacterium granulomatis.

Minocycline is indicated for treatment of infections caused by the following gram-negative microorganisms, when bacteriologic testing indicates appropriate susceptibility to the drug:

- Escherichia coli.
- Enterobacter aerogenes.
- Shigella species.
- Acinetobacter species.
- Respiratory tract infections caused by Haemophilus influenzae.
- Respiratory tract and urinary tract infections caused by Klebsiella species.

Minocycline hydrochloride tablets are indicated for the treatment of infections caused by the following gram-positive microorganisms when bacteriologic testing indicates appropriate susceptibility to the drug:

- Upper respiratory tract infections caused by Streptococcus pneumoniae.
- Skin and skin structure infections caused by Staphylococcus aureus.(Note: Minocycline is not the drug of choice in the treatment of any type of staphylococcal infection.)

When penicillin is contraindicated, minocycline is an alternative drug in the treatment of the following infections:

- Uncomplicated urethritis in men due to Neisseria gonorrhoeaeand for the treatment of other gonococcal infections.
- Infections in women caused by Neisseria gonorrhoeae.
- Syphilis caused by Treponema pallidumsubspecies pallidum.
- Yaws caused by Treponema pallidumsubspecies pertenue.
- Listeriosis due to Listeria monocytogenes.
- Anthrax due to Bacillus anthracis.
- Vincent’s infection caused by Fusobacterium fusiforme.
- Actinomycosis caused by Actinomyces israelii.
- Infections caused by Clostridiumspecies.

In acute intestinal amebiasis,minocycline may be a useful adjunct to amebicides.

In severe acne, minocycline may be useful adjunctive therapy.

Oral minocycline is indicated in the treatment of asymptomatic carriers of Neisseria meningitidisto eliminate the meningococci from the nasopharynx. In order to preserve the usefulness of minocycline in the treatment of asymptomatic meningococcal carriers, diagnostic laboratory procedures, including serotyping and susceptibility testing, should be performed to establish the carrier state and the correct treatment. It is recommended that the prophylactic use of minocycline be reserved for situations in which the risk of meningococcal meningitis is high.

Oral minocyclineis not indicated for the treatment of meningococcal infection.

Although no controlled clinical efficacy studies have been conducted, limited clinical data show that oral minocycline hydrochloride has been used successfully in the treatment of infections caused by Mycobacterium marinum.

To reduce the development of drug-resistant bacteria and maintain the effectiveness of minocycline hydrochloride tablets and other antibacterial drugs, minocycline hydrochloride tablets should be used only to treat or prevent infections that are proven or strongly suspected to be caused by susceptible bacteria. When culture and susceptibility information are available, they should be considered in selecting or modifying antimicrobial therapy. In the absence of such data, local epidemiology and susceptibility patterns may contribute to the empiric selection of therapy.

CONTRAINDICATIONS

This drug is contraindicated in persons who have shown hypersensitivity to any of the tetracyclines or to any of the components of the product formulation.

WARNINGS

MINOCYCLINE HYDROCHLORIDE TABLETS, LIKE OTHER TETRACYCLINES-CLASS ANTIBIOTICS, CAN CAUSE FETAL HARM WHEN ADMINISTERED TO A PREGNANT WOMAN. IF ANY TETRACYCLINE IS USED DURING PREGNANCY OR IF THE PATIENT BECOMES PREGNANT WHILE TAKING THESE DRUGS, THE PATIENT SHOULD BE APPRISED OF THE POTENTIAL HAZARD TO THE FETUS. THE USE OF DRUGS OF THE TETRACYCLINE CLASS DURING TOOTH DEVELOPMENT (LAST HALF OF PREGNANCY, INFANCY, AND CHILDHOOD TO THE AGE OF 8 YEARS) MAY CAUSE PERMANENT DISCOLORATION OF THE TEETH (YELLOW-GRAY-BROWN).

This adverse reaction is more common during long-term use of the drug but has been observed following repeated short-term courses. Enamel hypoplasia has also been reported. TETRACYCLINE DRUGS, THEREFORE, SHOULD NOT BE USED DURING TOOTH DEVELOPMENT UNLESS OTHER DRUGS ARE NOT LIKELY TO BE EFFECTIVE OR ARE CONTRAINDICATED.

All tetracyclines form a stable calcium complex in any bone-forming tissue. A decrease in fibula growth rate has been observed in premature human infants given oral tetracycline in doses of 25 mg/kg every six hours. This reaction was shown to be reversible when the drug was discontinued.

Results of animal studies indicate that tetracyclines cross the placenta, are found in fetal tissues, and can have toxic effects on the developing fetus (often related to retardation of skeletal development). Evidence of embryotoxicity has been noted in animals treated early in pregnancy.

Drug Rash with Eosinophilia and Systemic Symptoms (DRESS) including fatal cases have been reported with minocycline use. If this syndrome is recognized, the drug should be discontinued immediately.

The anti-anabolic action of the tetracyclines may cause an increase in BUN. While this is not a problem in those with normal renal function, in patients with significantly impaired function, higher serum levels of tetracycline may lead to azotemia, hyperphosphatemia, and acidosis. Under such conditions, monitoring of creatinine and BUN is recommended, and the total daily dosage should not exceed 200 mg in 24 hours (see DOSAGE AND ADMINISTRATION). If renal impairment exists, even usual oral or parenteral doses may lead to systemic accumulation of the drug and possible liver toxicity.

Photosensitivity manifested by an exaggerated sunburn reaction has been observed in some individuals taking tetracyclines. This has been reported with minocycline.

Central nervous system side effects including light headedness, dizziness, or vertigo have been reported with minocycline therapy. Patients who experience these symptoms should be cautioned about driving vehicles or using hazardous machinery while on minocycline therapy. These symptoms may disappear during therapy and usually disappear rapidly when the drug is discontinued.

Clostridium difficileassociated diarrhea (CDAD) has been reported with use of nearly all antibacterial agents, including minocycline hydrochloride, and may range in severity from mild diarrhea to fatal colitis. Treatment with antibacterial agents alters the normal flora of the colon leading to overgrowth of C. difficile.

C. difficileproduces toxins A and B which contribute to the development of CDAD. Hypertoxin producing strains of C. difficilecause increased morbidity and mortality, as these infections can be refractory to antimicrobial therapy and may require colectomy. CDAD must be considered in all patients who present with diarrhea following antibiotic use. Careful medical history is necessary since CDAD has been reported to occur over two months after the administration of antibacterial agents.

If CDAD is suspected or confirmed, ongoing antibiotic use not directed against C. difficilemay need to be discontinued. Appropriate fluid and electrolyte management, protein supplementation, antibiotic treatment of C. difficile,and surgical evaluation should be instituted as clinically indicated.

PRECAUTIONS

General

As with other antibiotic preparations, use of this drug may result in overgrowth of non-susceptible organisms, including fungi. If superinfection occurs, the antibiotic should be discontinued and appropriate therapy instituted.

Pseudotumor cerebri (benign intracranial hypertension) in adults has been associated with the use of tetracyclines. The usual clinical manifestations are headaches and blurred vision. Bulging fontanels have been associated with the use of tetracyclines in infants. While both of these conditions and related symptoms usually resolved after discontinuation of the tetracycline, the possibility for permanent sequelae exists.

Hepatotoxicity has been reported with minocycline; therefore, minocycline should be used with caution in patients with hepatic dysfunction and in conjunction with other hepatotoxic drugs.

Incision and drainage or other surgical procedures should be performed in conjunction with antibiotic therapy when indicated.

Prescribing minocycline hydrochloride tablets in the absence of a proven or strongly suspected bacterial infection or a prophylactic indication is unlikely to provide benefit to the patient and increases the risk of the development of drug resistant bacteria.

Information For Patients

Diarrhea is a common problem caused by antibiotics which usually ends when the antibiotic is discontinued. Sometimes after starting treatment with antibiotics, patients can develop watery and bloody stools (with or without stomach cramps and fever) even as late as two or more months after having taken the last dose of the antibiotic. If this occurs, patients should contact their physician as soon as possible.

Photosensitivity manifested by an exaggerated sunburn reaction has been observed in some individuals taking tetracyclines. Patients apt to be exposed to direct sunlight or ultraviolet light should be advised that this reaction can occur with tetracycline drugs, and treatment should be discontinued at the first evidence of skin erythema. This reaction has been reported with use of minocycline.

Patients who experience central nervous system symptoms should be cautioned about driving vehicles or using hazardous machinery while on minocycline therapy (see WARNINGS).

Concurrent use of tetracycline with oral contraceptives may render oral contraceptives less effective (see Drug Interactions).

Patients should be counseled that antibacterial drugs, including minocycline hydrochloride tablets should only be used to treat bacterial infections. They do not treat viral infections (e.g., the common cold). When minocycline hydrochloride tablets are prescribed to treat a bacterial infection, patients should be told that although it is common to feel better early in the course of therapy, the medication should be taken exactly as directed. Skipping doses or not completing the full course of therapy may: (1) decrease the effectiveness of the immediate treatment and (2) increase the likelihood that bacteria will develop resistance and will not be treatable by minocycline hydrochloride tablets or other antibacterial drugs in the future.

Unused supplies of tetracycline antibiotics should be discarded by the expiration date.

Laboratory Tests

In venereal disease when coexistent syphilis is suspected, a dark-field examination should be done before treatment is started and the blood serology repeated monthly for at least four months.

Periodic laboratory evaluations of organ systems, including hematopoietic, renal, and hepatic, should be performed.

Drug Interactions

Because tetracyclines have been shown to depress plasma prothrombin activity, patients who are on anticoagulant therapy may require downward adjustment of their anticoagulant dosage.

Since bacteriostatic drugs may interfere with the bactericidal action of penicillin, it is advisable to avoid giving tetracycline-class drugs in conjunction with penicillin.

Absorption of tetracyclines is impaired by antacids containing aluminum, calcium or magnesium, and iron-containing preparations.

The concurrent use of tetracycline and methoxyflurane has been reported to result in fatal renal toxicity.

Concurrent use of tetracyclines with oral contraceptives may render oral contraceptives less effective.

Administration of isotretinoin should be avoided shortly before, during, and shortly after minocycline therapy. Each drug alone has been associated with pseudotumor cerebri (see PRECAUTIONS).

Increased risk of ergotism when ergot alkaloids or their derivatives are given with tetracyclines.

Drug/ Laboratory Test Interactions

False elevations of urinary catecholamine levels may occur due to interference with the fluorescence test.

Carcinogenesis, Mutagenesis, Impairment of Fertility

Dietary administration of minocycline in long term tumorigenicity studies in rats resulted in evidence of thyroid tumor production. Minocycline has also been found to produce thyroid hyperplasia in rats and dogs. In addition, there has been evidence of oncogenic activity in rats in studies with a related antibiotic, oxytetracycline (i.e., adrenal and pituitary tumors). Likewise, although mutagenicity studies of minocycline have not been conducted, positive results in in vitromammalian cell assays (i.e., mouse lymphoma and Chinese hamster lung cells) have been reported for related antibiotics (tetracycline hydrochloride and oxytetracycline). Segment I (fertility and general reproduction) studies have provided evidence that minocycline impairs fertility in male rats.

Pregnancy

Teratogenic Effects: Pregnancy Category D(See WARNINGS).

All pregnancies have a background risk of birth defects, loss, or other adverse outcome regardless of drug exposure. There are no adequate and well-controlled studies on the use of minocycline in pregnant women. Minocycline, like other tetracycline-class antibiotics, crosses the placenta and may cause fetal harm when administered to a pregnant woman. Rare spontaneous reports of congenital anomalies including limb reduction have been reported in post-marketing experience. Only limited information is available regarding these reports; therefore, no conclusion on causal association can be established. If minocycline is used during pregnancy or if the patient becomes pregnant while taking this drug, the patient should be apprised of the potential hazard to the fetus.

Nonteratogenic Effects(See WARNINGS).

Labor and Delivery

The effect of tetracyclines on labor and delivery is unknown.

Nursing Mothers

Tetracyclines are excreted in human milk. Because of the potential for serious adverse reactions in nursing infants from the tetracyclines, a decision should be made whether to discontinue nursing or discontinue the drug, taking into account the importance of the drug to the mother (see WARNINGS).

Pediatric Use

Minocycline is not recommended for use in children below 8 years of age unless the expected benefits of therapy outweigh the risks (see WARNINGS).

Geriatric Use

Clinical studies of oral minocycline did not include sufficient numbers of subjects aged 65 and over to determine whether they respond differently from younger subjects. In general, dose selection for an elderly patient should be cautious, usually starting at the low end of the dosing range, reflecting the greater frequency of decreased hepatic, renal, or cardiac function, and of concomitant disease or other drug therapy (see WARNINGS, DOSAGE AND ADMINISTRATION).

ADVERSE REACTIONS

Due to oral minocycline’s virtually complete absorption, side effects to the lower bowel, particularly diarrhea, have been infrequent. The following adverse reactions have been observed in patients receiving tetracyclines.

Body as a whole: Fever, and discoloration of secretions.

Gastrointestinal: Anorexia, nausea, vomiting, diarrhea, dyspepsia, stomatitis, glossitis, dysphagia, enamel hypoplasia, enterocolitis, pseudomembranous colitis, pancreatitis, inflammatory lesions (with monilial overgrowth) in the oral and anogenital regions. Instances of esophagitis and esophageal ulcerations have been reported in patients taking the tetracycline-class antibiotics in capsule and tablet form. Most of these patients took the medication immediately before going to bed (see DOSAGE AND ADMINISTRATION) .

Genitourinary: Vulvovaginitis.

Hepatic toxicity: Hyperbilirubinemia, hepatic cholestasis, increases in liver enzymes, fatal hepatic failure, and jaundice. Hepatitis, including autoimmune hepatitis, and liver failure have been reported (see PRECAUTIONS).

Skin: Alopecia, erythema nodosum, hyperpigmentation of nails, pruritus, toxic epidermal necrolysis, and vasculitis. Maculopapular and erythematous rashes. Exfoliative dermatitis has been reported. Fixed drug eruptions have been reported. Lesions occurring on the glans penis have caused balanitis. Erythema multiforme and Stevens-Johnson syndrome have been reported. Photosensitivity is discussed above (see WARNINGS). Pigmentation of the skin and mucous membranes has been reported.

Respiratory: Cough, dyspnea, bronchospasm, exacerbation of asthma, and pneumonitis.

Renal toxicity: Interstitial nephritis. Elevations in BUN have been reported and are apparently dose related (see WARNINGS). Reversible acute renal failure has been reported.

Musculoskeletal: Arthralgia, arthritis, bone discoloration, myalgia, joint stiffness, and joint swelling.

Hypersensitivity reactions: Urticaria, angioneurotic edema, polyarthralgia, anaphylaxis/anaphylactoid reaction (including shock and fatalities), anaphylactoid purpura, myocarditis, pericarditis, exacerbation of systemic lupus erythematosus and pulmonary infiltrates with eosinophilia have been reported. A transient lupus-like syndrome and serum sickness-like reactions have also been reported.

Blood: Agranulocytosis, hemolytic anemia, thrombocytopenia, leukopenia, neutropenia, pancytopenia, and eosinophilia have been reported.

Central Nervous System: Convulsions, dizziness, hypesthesia, paresthesia, sedation, and vertigo. Bulging fontanels in infants and benign intracranial hypertension (pseudotumor cerebri) in adults have been reported (see PRECAUTIONS-General). Headache has also been reported.

Other: Thyroid cancer has been reported in the post-marketing setting in association with minocycline products. When minocycline therapy is given over prolonged periods, monitoring for signs of thyroid cancer should be considered. When given over prolonged periods, tetracyclines have been reported to produce brown-black microscopic discoloration of the thyroid gland. Cases of abnormal thyroid function have been reported.

Tooth discoloration in children less than 8 years of age and also in adults, has been reported (see WARNINGS).

Oral cavity discoloration (including tongue, lip, and gum) have been reported.

Tinnitus and decreased hearing have been reported in patients on minocycline hydrochloride.

The following syndromes have been reported. In some cases involving these syndromes, death has been reported. As with other serious adverse reactions, if any of these syndromes are recognized, the drug should be discontinued immediately:

Hypersensitivity syndrome consisting of cutaneous reaction (such as rash or exfoliative dermatitis), eosinophilia, and one or more of the following: hepatitis, pneumonitis, nephritis, myocarditis, and pericarditis. Fever and lymphadenopathy may be present.

Lupus-like syndrome consisting of positive antinuclear antibody; arthralgia, arthritis, joint stiffness, or joint swelling; and one or more of the following: fever, myalgia, hepatitis, rash, and vasculitis.

Serum sickness-like syndrome consisting of fever; urticaria or rash; and arthralgia, arthritis, joint stiffness, or joint swelling. Eosinophilia may be present.

OVERDOSAGE

The adverse events more commonly seen in overdose are dizziness, nausea, and vomiting.

No specific antidote for minocycline is known.

In case of overdosage, discontinue medication, treat symptomatically and institute supportive measures. Minocycline is not removed in significant quantities by hemodialysis or peritoneal dialysis.

DOSAGE AND ADMINISTRATION

THE USUAL DOSAGE AND FREQUENCY OF ADMINISTRATION OF MINOCYCLINE DIFFERS FROM THAT OF THE OTHER TETRACYCLINES. EXCEEDING THE RECOMMENDED DOSAGE MAY RESULT IN AN INCREASED INCIDENCE OF SIDE EFFECTS.

Minocycline hydrochloride tablets may be taken with or without food (see CLINICAL PHARMACOLOGY).

Ingestion of adequate amounts of fluids along with capsule and tablet forms of drugs in the tetracycline-class is recommended to reduce the risk of esophageal irritation and ulceration. The tablets should be swallowed whole.

For Pediatric Patients Above 8 Years of Age

Usual pediatric dose: 4 mg/kg initially followed by 2 mg/kg every 12 hours, not to exceed the usual adult dose.

Adults

The usual dosage of minocycline hydrochloride tablets is 200 mg initially followed by 100 mg every 12 hours. Alternatively, if more frequent doses are preferred, two or four 50 mg tablets may be given initially followed by one 50 mg tablet four times daily.

Uncomplicated gonococcal infections other than urethritis and anorectal infections in men: 200 mg initially, followed by 100 mg every 12 hours for a minimum of four days, with post-therapy cultures within 2 to 3 days.

In the treatment of uncomplicated gonococcal urethritis in men, 100 mg every 12 hours for 5 days is recommended.

For the treatment of syphilis, the usual dosage of minocycline hydrochloride should be administered over a period of 10 to 15 days. Close follow-up, including laboratory tests, is recommended.

In the treatment of meningococcal carrier state, the recommended dosage is 100 mg every 12 hours for five days.

Mycobacterium marinuminfections: Although optimal doses have not been established, 100 mg every 12 hours for 6 to 8 weeks have been used successfully in a limited number of cases.

Uncomplicated urethral, endocervical, or rectal infection in adults caused by Chlamydia trachomatis or Ureaplasma urealyticum:100 mg orally, every 12 hours for at least seven days.

Ingestion of adequate amounts of fluids along with capsule and tablet forms of drugs in the tetracycline-class is recommended to reduce the risk of esophageal irritation and ulceration.

The pharmacokinetics of minocycline in patients with renal impairment (CLCR <80mL/min) have not been fully characterized. Current data are insufficient to determine if a dosage adjustment is warranted. The total daily dosage should not exceed 200 mg in 24 hours. However, due to the anti-anabolic effect of tetracyclines, BUN and creatinine should be monitored (see WARNINGS).

HOW SUPPLIED

Minocycline Hydrochloride Tablets, USP are supplied as aqueous film-coated tablets containing minocycline hydrochloride equivalent to 50 mg, 75 mg and 100 mg minocycline.

The 50 mg tablets are off white to cream color, round, film-coated tablets with “CE”above “236”debossed on one side and plain on the other side.

(NDC 62135-887-90) Bottle of 90 Tablets

The 75 mg tablets are off white to cream color, round, film-coated tablets with “CE”above “237”debossed on one side and plain on the other side.

(NDC 62135-888-60) Bottle of 60 Tablets

The 100 mg tablets are off white to cream color, round, film-coated tablets with “CE”above “238”debossed on one side and plain on the other side.

(NDC 62135-889-60) Bottle of 60 Tablets

Store between 20ºC to 25ºC (68ºF to 77ºF) [See USP Controlled Room Temperature].

Protect from light, moisture and excessive heat.

Dispense in a tight, light-resistant container as defined in the USP.

ANIMAL PHARMACOLOGY AND TOXICOLOGY

Minocycline hydrochloride has been observed to cause a dark discoloration of the thyroid in experimental animals (rats, minipigs, dogs and monkeys). In the rat, chronic treatment with minocycline hydrochloride has resulted in goiter accompanied by elevated radioactive iodine uptake and evidence of thyroid tumor production. Minocycline hydrochloride has also been found to produce thyroid hyperplasia in rats and dogs.

REFERENCES

1. National Committee for Clinical Laboratory Standards, Methods for Dilution Antimicrobial Susceptibility Tests for Bacteria that Grow Aerobically - Fourth Edition; Approved Standard. NCCLS Document M7- A4, Vol. 17, No. 2, NCCLS, 940 West Valley Road, Suite 1400, Wayne, PA. January 1997.
2. National Committee for Clinical Laboratory Standards, Performance Standards for Antimicrobial Disk Susceptibility Tests - Sixth Edition; Approved Standard. NCCLS Document M2-A6, Vol. 17, No. 1, NCCLS, 940 West Valley Road, Suite 1400, Wayne, PA. January 1997.
3. National Committee for Clinical Laboratory Standards, Performance Standards for Antimicrobial Disk Susceptibility Tests - Eighth Edition; Approved Standard. NCCLS Document M100-S8, Vol. 18, No. 1, NCCLS, 940 West Valley Road, Suite 1400, Wayne, PA. January 1998.

Manufactured for:
Chartwell RX, LLC
Congers, NY10920
L72675
Rev. 06/2025

PATIENT INFORMATION

Minocycline Hydrochloride Tablets USP, 50 mg, 75 mg, and 100 mg

(mye-no-SYE-kleen)

Read the Patient Information that comes with Minocyline Hydrochloride Tablets before you or a family member starts taking it and each time you get a refill. There may be new information. This leaflet does not take the place of talking to your doctor about your medical condition or treatment.

What is Minocycline Hydrochloride?

Minocycline Hydrochloride is a tetracycline-class antibiotic medicine. Minocycline Hydrochloride is used to treat certain infections caused by bacteria. These include infections of the skin, respiratory tract, urinary tract, some sexually transmitted diseases, and others. Minocycline Hydrochloride may be used along with other treatments for severe acne.

Sometimes, other germs, called viruses cause infections. The common cold is a virus. Minocycline Hydrochloride, like other antibiotics, does not treat viruses.

Who should not use Minocycline Hydrochloride?

Do not take Minocycline Hydrochloride if you are allergic to minocycline or other tetracycline antibiotics.
Ask your doctor or pharmacist for a list of these medications if you are not sure. See the end of this leaflet for a complete list of ingredients in Minocycline Hydrochloride.

Minocycline Hydrochloride is not recommended for pregnant women or children up to 8 years old because:

1. Minocycline Hydrochloride may harm an unborn baby.
2. Minocycline Hydrochloride may permanently turn a baby’s or child’s teeth yellow-gray-brown during tooth development.Tooth development happens in the last half of pregnancy and birth to age 8 years.

What should I tell my doctor before starting Minocycline Hydrochloride Tablets?

Tell your doctor about all of your medical conditions, including if you:

- have liver or kidney problems.
- are pregnant or planning to become pregnant.Minocycline Hydrochloride may harm your unborn baby. Stop taking Minocycline Hydrochloride and call your doctor if you become pregnant while taking it
- are breast feeding.Minocycline Hydrochloride passes into your milk and may harm your baby. You should decide whether to use Minocycline Hydrochloride or breastfeed, but not both.

Tell your doctor about all the medicines you are taking including prescription and non- prescription medications, vitamins, and herbal supplements. Minocycline Hydrochloride and other medicines may interact. Especially tell your doctor if you take:

- birth control pills.Minocycline Hydrochloride may make your birth control pills less effective.
- a blood thinner medicine.The dose of your blood thinner may have to be lowered.
- a penicillin antibiotic medicine.Minocycline Hydrochloride and penicillins should not be used together.
- Migraine medicines called ergot alkaloids.
- An acne medicine called isotretinoin (Accutane®, Amnesteem®, Claravis®, Sotret®).
- Antacids that contain aluminum, calcium, or magnesium, or iron-containing products.

Know the medicines you take, keep a list of them to show your doctor and pharmacist each time you get a new medicine.

How should I take Minocycline Hydrochloride Tablets?

- Take Minocycline Hydrochloride Tablets exactly as your doctor tells you to take them.Skipping doses or not taking all your Minocycline Hydrochloride may:
- Decrease the effectiveness of the treatment.
- Increase the chance that bacteria will develop resistance to Minocycline Hydrochloride.
- Take Minocycline Hydrochloride with a full glass of liquid.Taking Minocycline Hydrochloride with enough liquid may lower your chance of getting irritation or ulcers in your esophagus. Your esophagus is the tube that connects your mouth to your stomach.
- Minocycline Hydrochloride Tablets may be taken with or without food. If you forget to take Minocycline Hydrochloride, take it as soon as you remember.
- If you take too much Minocycline Hydrochloride, call you doctor or poison control center right away.

What are the possible side effects of Minocycline Hydrochloride?

Minocycline Hydrochloride may cause serious side effects. Stop Minocycline Hydrochloride and call your doctor if you have:

- watery diarrhea
- bloody stools
- Stomach cramps
- unusual headaches
- blurred vision
- fever
- rash
- joint pain
- feeling very tired

Minocycline Hydrochloride may also cause:

- central nervous system effects.Symptoms include light-headedness, dizziness, and aspinning feeling (vertigo). You should not drive or operate machines if you have these symptoms.
- sun sensitivity (photosensitivity).You may get a worse sunburn with MinocyclineHydrochloride. Avoid sun exposure and the use of sunlamps or tanning beds. Protect your skin while out in the sunlight. Stop Minocycline Hydrochloride and call your doctor if your skin turns red.

These are not all the side effects with Minocycline Hydrochloride. Ask your doctor or pharmacist for more information.

How should I store Minocycline Hydrochloride Tablets?

- Store Minocycline Hydrochloride Tablets at room temperature and away from excess heatand moisture.
- Throw away any Minocycline Hydrochloride that is outdated or no longer needed.
- Keep Minocycline Hydrochloride Tablets and all medicines out of the reach of children.

General advice about Minocycline Hydrochloride Tablets

Medicines are sometimes prescribed for purposes other than those listed in a Patient Information leaflet. Do not use Minocycline Hydrochloride Tablets for a condition for which it was not prescribed. Do not give Minocycline Hydrochloride Tablets to other people, even if they have the same symptoms you have. It may harm them.

This Patient Information leaflet summarizes the most important information about Minocycline Hydrochloride. If you would like more information, talk with your doctor.

Your doctor or pharmacist can give you information about Minocycline Hydrochloride that is written for health care professionals. For more information, you can also call Chartwell RX, LLC at 845-232-1683. Call your doctor for medical advice about side effects. You may report side effects to FDA at 1-800-FDA-1088.

What are the ingredients in Minocycline Hydrochloride Tablets?

Active ingredient:minocycline hydrochloride

Inactive ingredients:lactose monohydrate, magnesium stearate, microcrystalline cellulose, povidone, sodium starch glycolate, titanium dioxide, hypromellose, polyethylene glycol 400, and polysorbate 80.

Manufactured for:
Chartwell RX, LLC
Congers, NY10920
L72676
Rev. 06/2025

PRINCIPAL DISPLAY PANEL

Minocycline Hydrochloride Tablets, USP 50mg - NDC 62135-887-90 - 90 Tabs Bottle Label

Minocycline Hydrochloride Tablets, USP 75mg - NDC 62135-888-60 - 60 Tabs Bottle Label

Minocycline Hydrochloride Tablets, USP 100mg - NDC 62135-889-60 - 60 Tabs Bottle Label